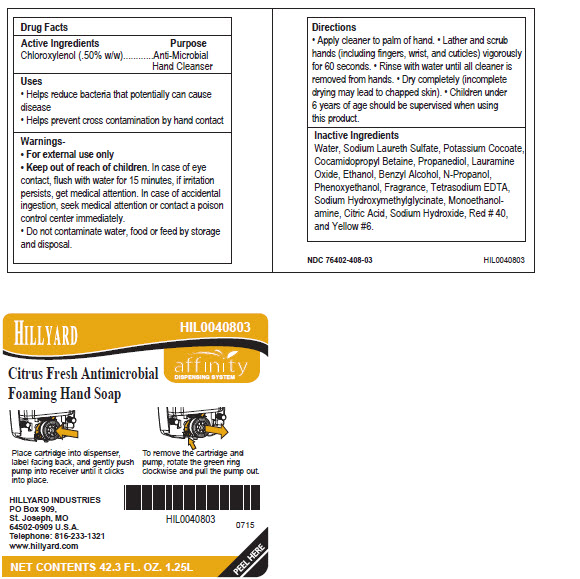 DRUG LABEL: Hillyard Citrus Fresh Antimicrobial Foaming
NDC: 76402-408 | Form: LIQUID
Manufacturer: Hillyard GMP
Category: otc | Type: HUMAN OTC DRUG LABEL
Date: 20241230

ACTIVE INGREDIENTS: CHLOROXYLENOL 0.50 g/100 mL
INACTIVE INGREDIENTS: WATER; SODIUM LAURETH-3 SULFATE; POTASSIUM COCOATE; COCAMIDOPROPYL BETAINE; PROPANEDIOL; LAURAMINE OXIDE; ALCOHOL; BENZYL ALCOHOL; PROPYL ALCOHOL; PHENOXYETHANOL; EDETATE SODIUM; SODIUM HYDROXYMETHYLGLYCINATE; 2-AMINOETHANOL; ANHYDROUS CITRIC ACID; SODIUM HYDROXIDE; FD&C RED NO. 40; FD&C YELLOW NO. 6

Hillyard Citrus Fresh Antimicrobial Foaming Hand Soap

Active ingredient

Chloroxylenol (.50% w/w)

Purpose

Anti-Microbial Hand Cleanser

Uses

- Helps reduce bacteria that potentially can cause disease
- Helps prevent cross contamination by hand contact

Warnings

- For External Use Only
- Do not contaminate water, food or feed by storage and disposal.

Keep Out of Reach of Children

- In case of eye contact, flush with water for 15 minutes, if irritation persists, get medical attention. In case of accidental ingestion, seek medical attention or contact a poison control center immediately.

Directions

- Apply cleaner to palm of hand.
- Lather and scrub hands (including fingers, wrist, and cuticles) vigorously for 60 seconds.
- Rinse with water until all cleaner is removed from hands.
- Dry completely (incomplete drying may lead to chapped skin).
- Children under 6 years of age should be supervised when using this product.

Inactive Ingredients

Water, Sodium Laureth Sulfate, Potassium Cocoate, Cocamidopropyl Betaine, Propanediol, Lauramine Oxide, Ethanol, Benzyl Alcohol, N-Propanol, Phenoxyethanol, Fragrance, Tetrasodium EDTA, Sodium Hydroxymethylglycinate, Monoethanolamine, Citric Acid, Sodium Hydroxide, Red #40, and Yellow #6.

Package/Label Principal Display Panel

Hillyard
Citrus Fresh Antimicrobial
Foaming Hand Soap

HIL0040803

affinity
DISPENSING SYSTEM

Place cartridge into dispenser, label facing back, and gently push pump into receiver until it clicks into place.

To remove the cartridge and pump, rotate the green ring clockwise and pull the pump out.

HILLYARD INDUSTRIES
PO Box 909,
St. Joseph, MO
64502-0909 U.S.A.
Telephone: 816-233-1321
www.hillyard.com

NET CONTENTS 42.3 FL. OZ. 1.25L
PEEL HERE

Carton Label